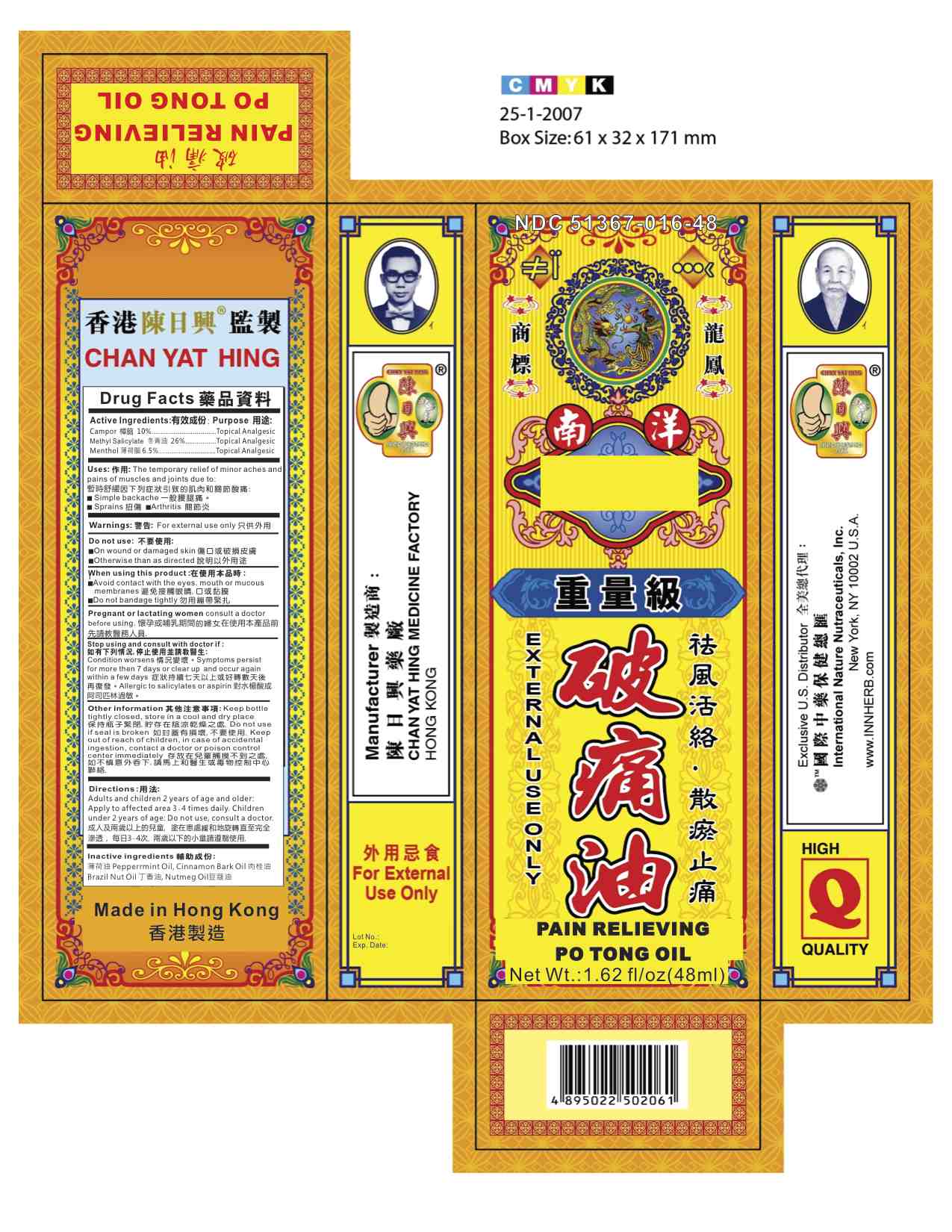 DRUG LABEL: Pain Relieving Po Tong Oil
NDC: 51367-016 | Form: OIL
Manufacturer: International Nature Nutraceuticals
Category: otc | Type: HUMAN OTC DRUG LABEL
Date: 20131020

ACTIVE INGREDIENTS: CAMPHOR (NATURAL) 4.64 g/1 1; METHYL SALICYLATE 14.65 g/1 1; MENTHOL 2.78 g/1 1
INACTIVE INGREDIENTS: PEPPERMINT OIL; CINNAMON BARK OIL; BRAZIL NUT OIL; NUTMEG OIL

Drug Facts

Active Ingredients

Camphor- 10%

Methyl Salicylate- 26%

Menthol- 6.5%

Uses:

The temporary relief of minor aches and

pains of muscles and joints due to:

暫時舒緩因下列症狀引致的肌肉和關節酸痛:

Simple backache 一般腰腿痛。

Sprains 扭傷 Arthritis 關節炎

Warnings:

For external use only

Do Not Use:

On wound or damaged skin 傷口或破損皮膚

Otherwise than as directed 說明以外用途

Stop Using and Consult with a doctor if:

Condition worsens 情況變壞。Symptoms persist

for more then 7 days or clear up and occur again

within a few days 症狀持續七天以上或好轉數天後

再復發。Allergic to salicylates or aspirin 對水楊酸或

阿司匹林過敏。

Keep out of reach of children

In case of accidental ingestion, contact a doctor or posion control center immediately.

Directions

Adults and children 2 years of age and older:

Apply to affected area 3-4 times daily. Children

under 2 years of age: Do not use, consult a doctor.

成人及兩歲以上的兒童, 塗在患處緩和地旋轉直至完全

滲透， 每日3-4次. 兩歲以下的小童請遵翳使用.

When Using this product:

Avoid contact with the eyes. mouth or mucous

membranes 避免接觸眼睛,口或黏膜

Do not bandage tightly 勿用繃帶緊扎

Pregnant or lactating women consult a doctor

before using. 懷孕或哺乳期間的婦女在使用本產品前

先請教醫務人員.

Inactive Ingredients

薄荷油 Pepperrmint Oil, Cinnamon Bark Oil 肉桂油

Brazil Nut Oil 丁香油, Nutmeg Oil豆蔻油

Other Information:

Keep bottle tightly closed, store in a cool and dry place

保持瓶子緊閉,貯存在陰涼乾燥之處.Do not use

if seal is broken 如封蓋有損壞,不要使用